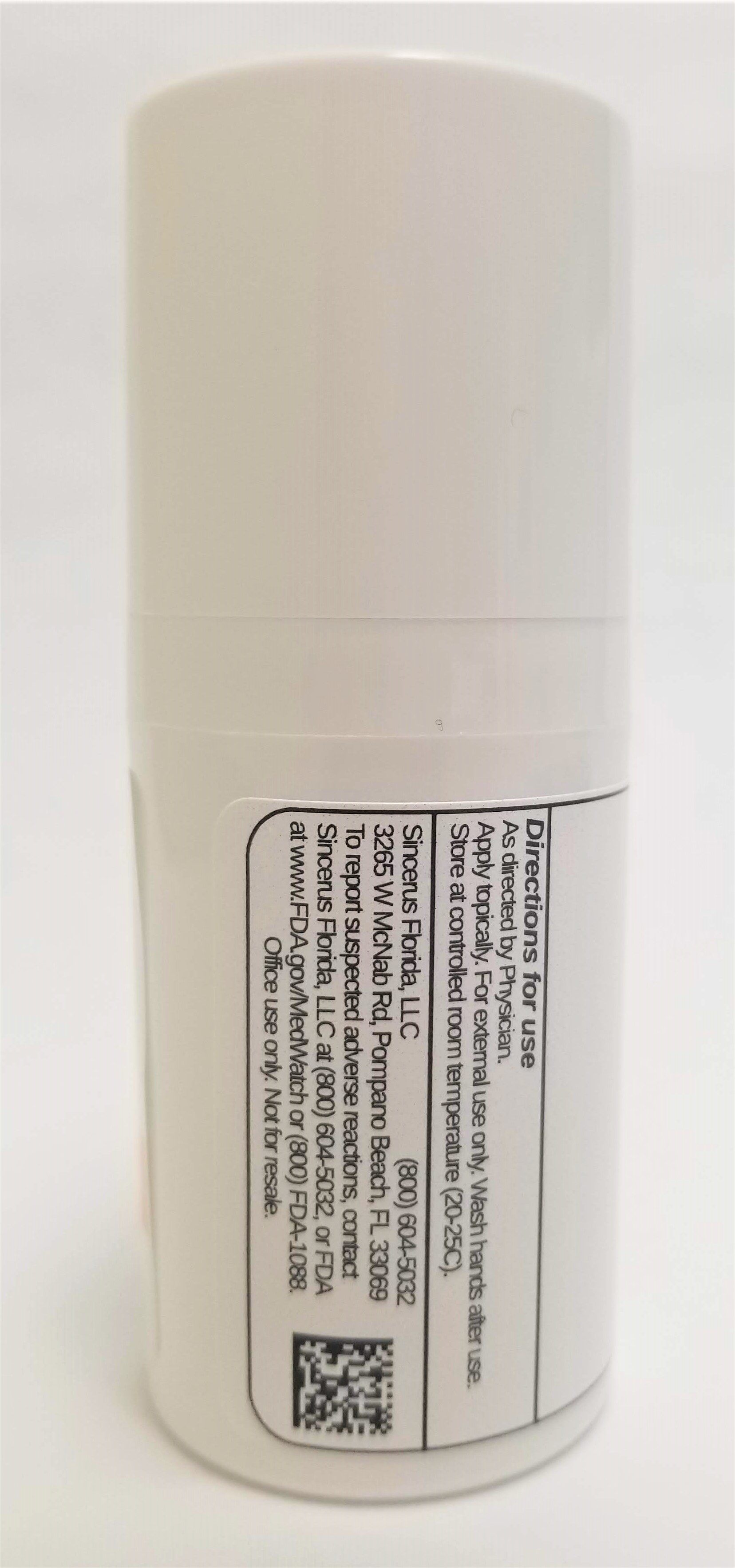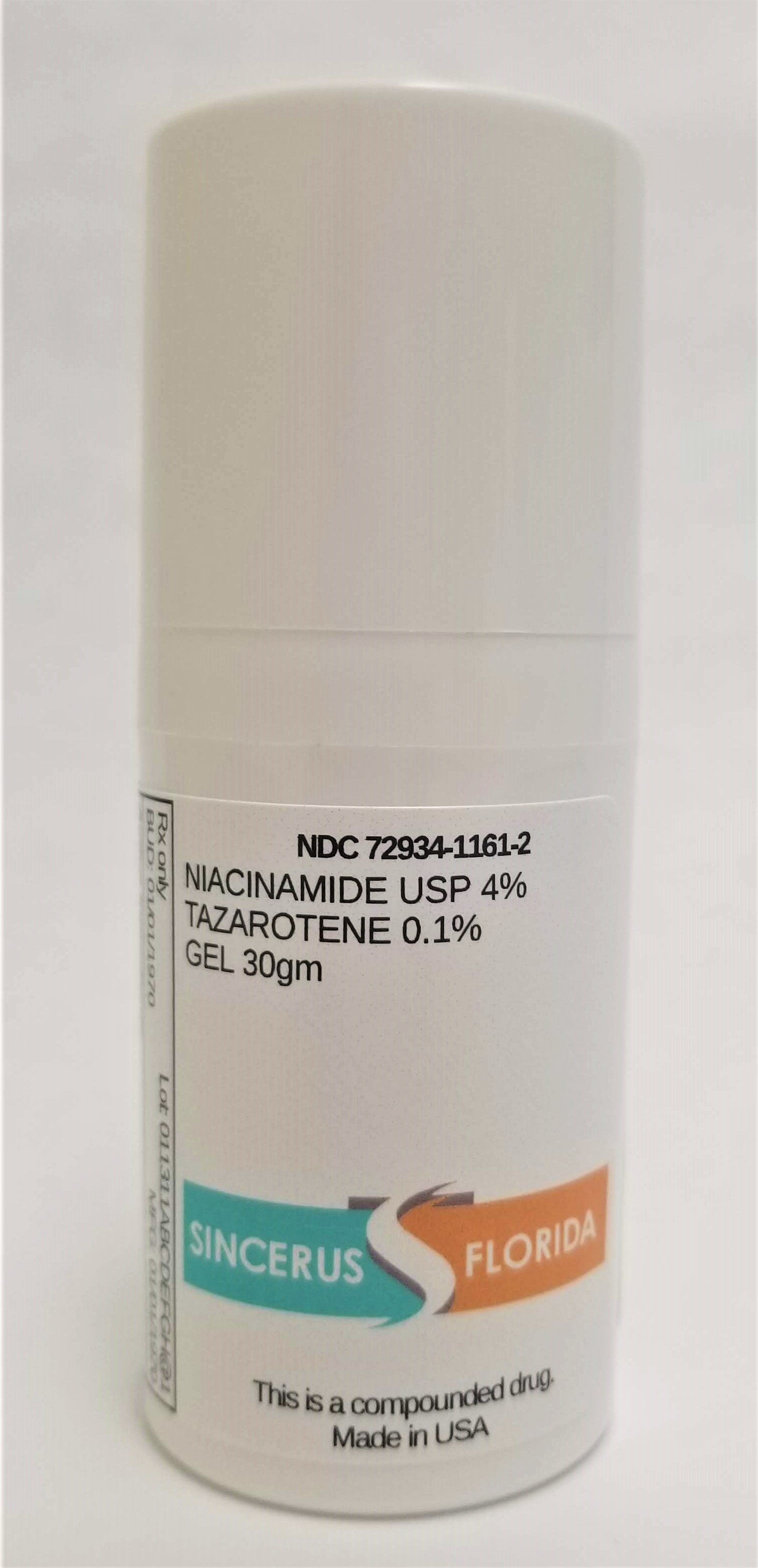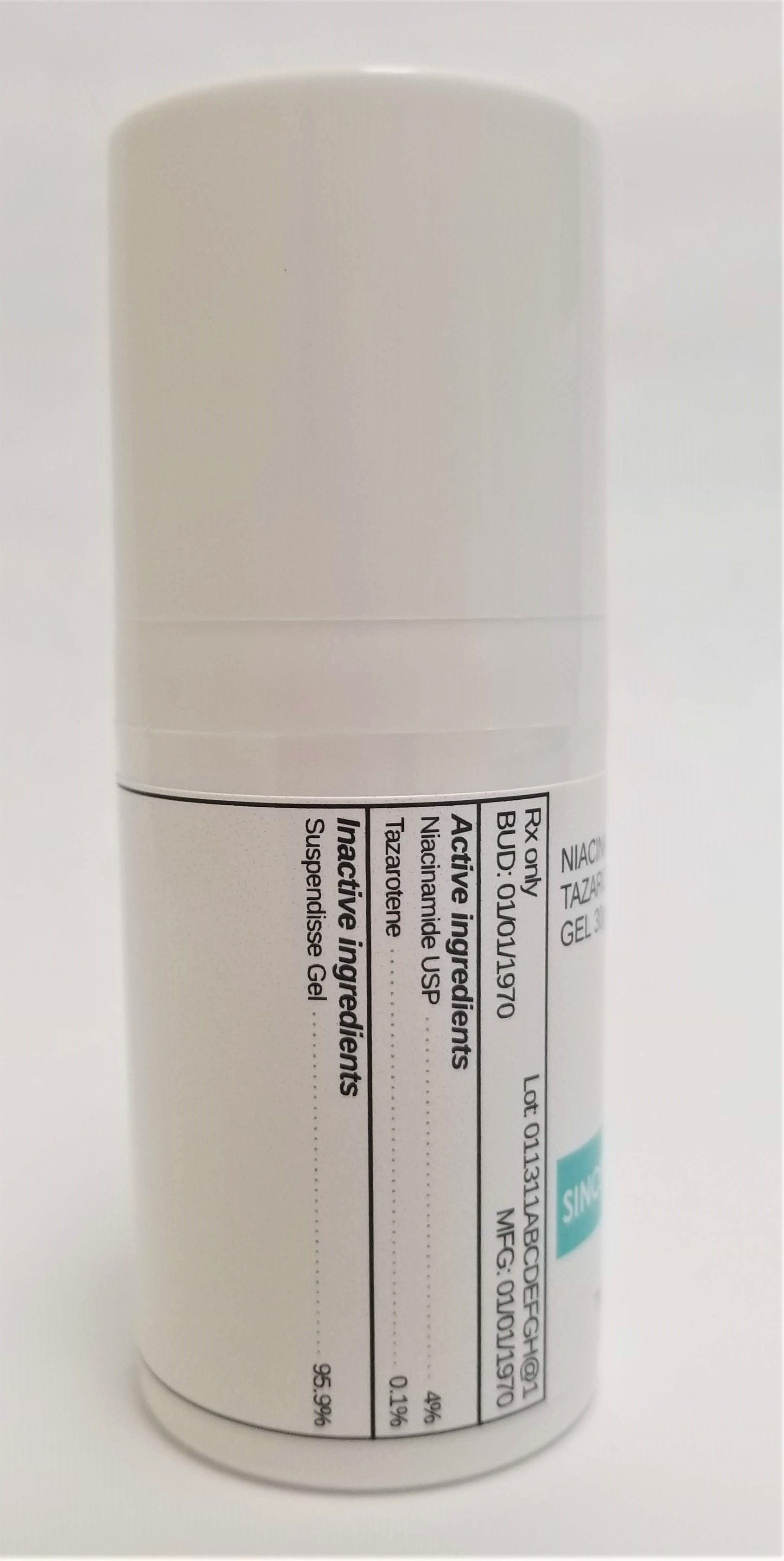 DRUG LABEL: NIACINAMIDE 4% / TAZAROTENE 0.1%
NDC: 72934-1161 | Form: GEL
Manufacturer: Sincerus Florida, LLC
Category: prescription | Type: HUMAN PRESCRIPTION DRUG LABEL
Date: 20190509

ACTIVE INGREDIENTS: NIACINAMIDE 4 g/100 g; TAZAROTENE 0.1 g/100 g

NIACINAMIDE 4% / TAZAROTENE 0.1%